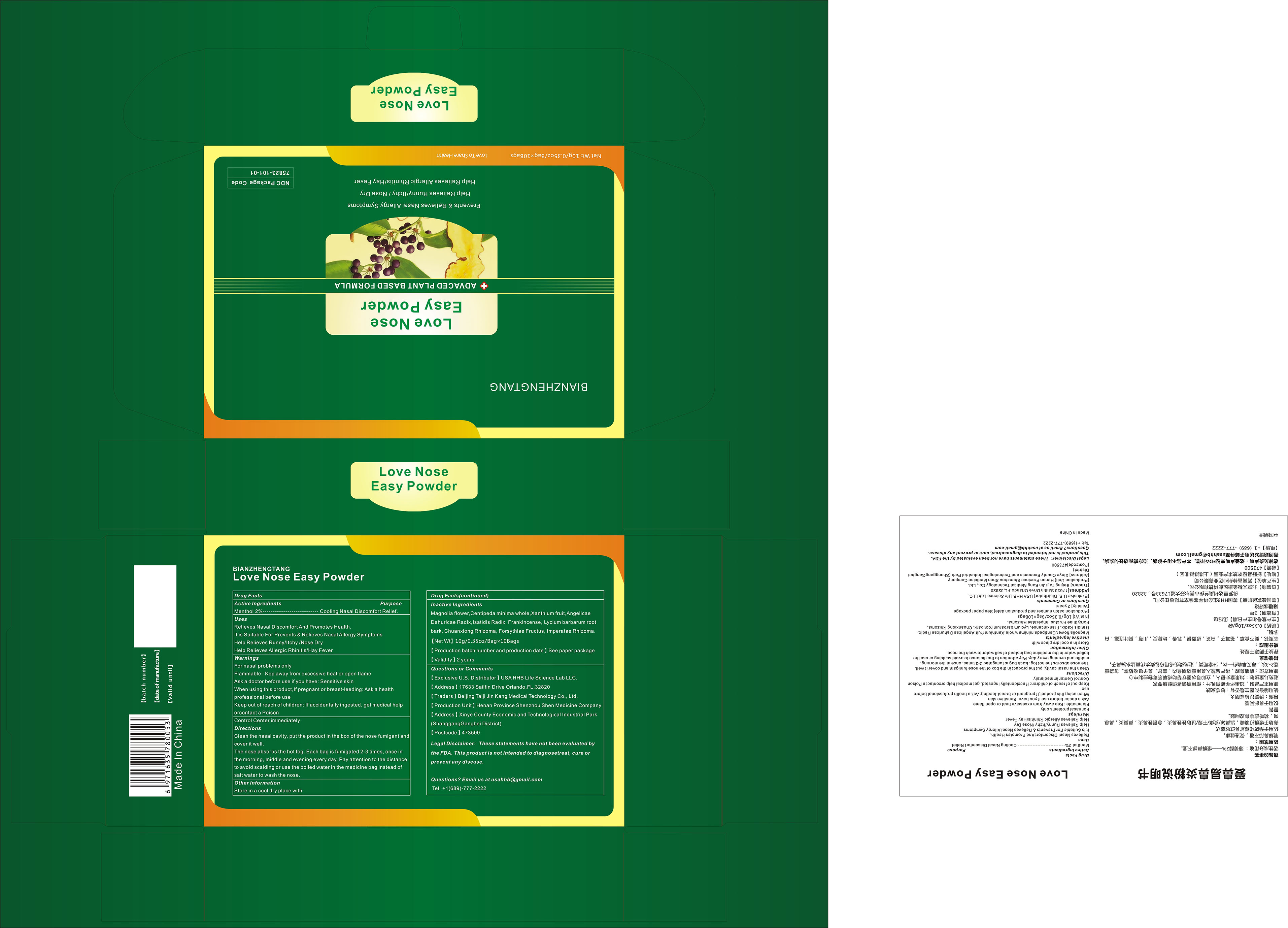 DRUG LABEL: Love Nose Easy Powder
NDC: 75823-101 | Form: POWDER
Manufacturer: Beijing Taiji Jin Kang Medical Technology Co., Ltd.
Category: otc | Type: HUMAN OTC DRUG LABEL
Date: 20200820

ACTIVE INGREDIENTS: MENTHOL 2 g/100 g
INACTIVE INGREDIENTS: FORSYTHIA SUSPENSA FRUIT; MAGNOLIA SPRENGERI FLOWER BUD; CENTIPEDA MINIMA WHOLE; XANTHIUM SIBIRICUM FRUIT; IMPERATA CYLINDRICA ROOT; ISATIS TINCTORIA ROOT; FRANKINCENSE; LYCIUM BARBARUM ROOT BARK; LIGUSTICUM WALLICHII ROOT; ANGELICA DAHURICA ROOT

101 Love Nose Easy Powder

Active Ingredients

Borneol 2%

Purpose

cooling Nasal discomfort relief

Uses

Relieves Nasal Discomfort And Promotes Health.
It is Suitable For Prevents & Relieves Nasal Allergy Symptoms
Help Relieves Runny/Itchy /Nose Dry
Help Relieves Allergic Rhinitis/Hay Fever

do not use

/

Precautions for use

For nasal problems only
Flammable : Kep away from excessive heat or open flame
Ask a doctor before use if you have: Sensitive skin
When using this product,lf pregnant or breast-leeding: Ask a health
professional before use

Storage

Store in a dry place at room temperature.

STOP USE

/

Keep out of reach of children: If accidentally ingested, get medical help orcontact a Poison Control Center immediately

INACTIVE INGREDIENT

Magnolia flower, Centipeda minima whole, Xanthium fruit, Angelicae Dahuricae Radix, Isatidis Radix, Frankincense, Lycium barbarum root bark, Chuanxiong Rhizoma, Forsythiae Fructus, Imperatae Rhizoma

Directions

Clean the nasal cavity, put the product in the box of the nose fumigant and cover it well.
The nose absorbs the hot fog. Each bag is fumigated 2-3 times, once in the morning, middle and evening every day. Pay attention to the distance to avoid scalding or use the boiled water in the medicine bag instead of salt water to wash the nose.